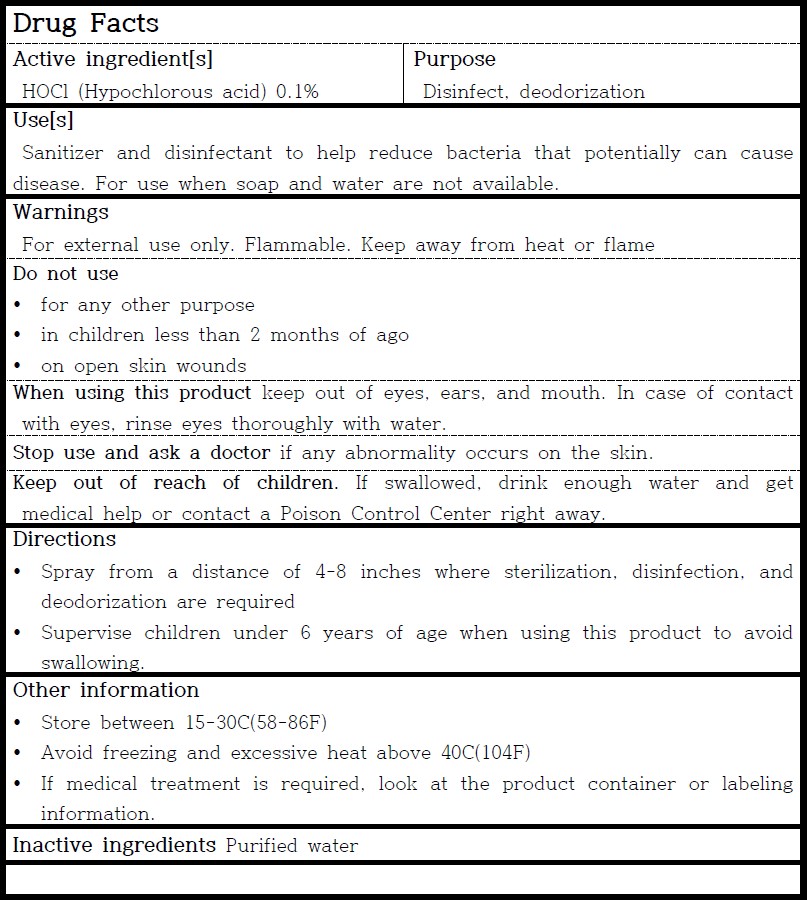 DRUG LABEL: Sufiya
NDC: 82124-701 | Form: LIQUID
Manufacturer: EMSOLUTION Co., Ltd
Category: otc | Type: HUMAN OTC DRUG LABEL
Date: 20221229

ACTIVE INGREDIENTS: HYPOCHLOROUS ACID 0.1 g/100 mL
INACTIVE INGREDIENTS: WATER

82124-701 Sufiya

Active ingredient[s]

HOCl (Hypochlorous acid) 0.1%

Purpose

Disinfect, deodorization

Use[s]

Sanitizer and disinfectant to help reduce bacteria that potentially can cause disease. For use when soap and water are not available.

Warnings

For external use only. Flammable. Keep away from heat or flame

Do not use

- for any other purpose
- in children less than 2 months of ago
- on open skin wounds

When using this product

keep out of eyes, ears, and mouth. In case of contact with eyes, rinse eyes thoroughly with water.

Stop use and ask a doctor

if any abnormality occurs on the skin.

Keep out of reach of children.

If swallowed, drink enough water and get medical help or contact a Poison Control Center right away.

Directions

- Spray from a distance of 4-8 inches where sterilization, disinfection, and deodorization are required
- Supervise children under 6 years of age when using this product to avoid swallowing.

Other information

- Store between 15-30C(58-86F)
- Avoid freezing and excessive heat above 40C(104F)
- If medical treatment is required, look at the product container or labeling information.

Inactive ingredients

Purified water